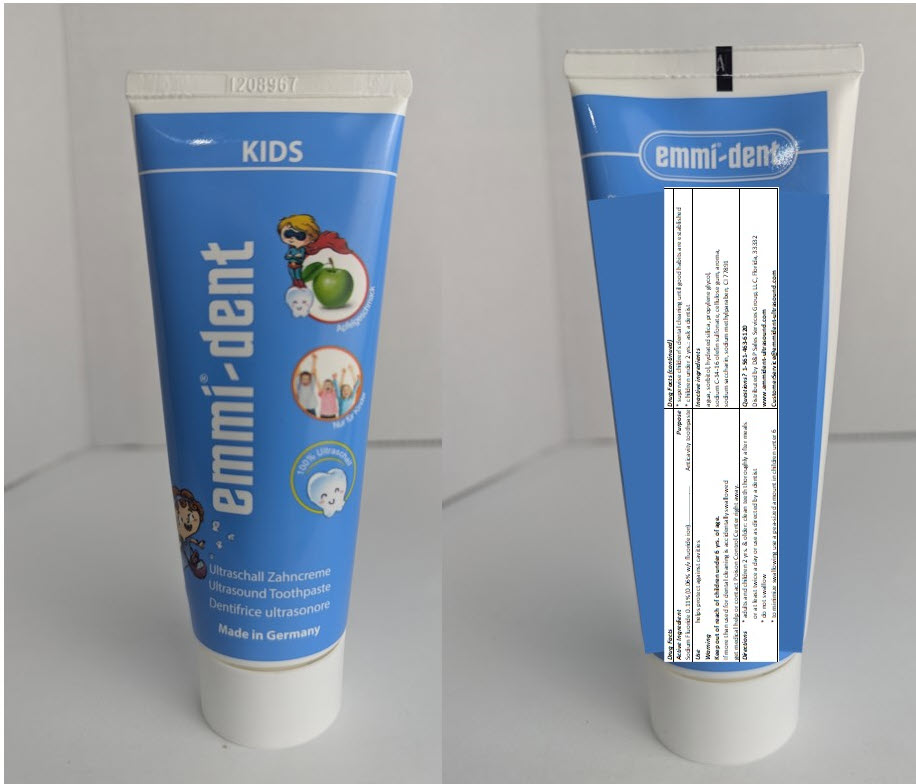 DRUG LABEL: Emmi-dent Kids
NDC: 63956-002 | Form: PASTE, DENTIFRICE
Manufacturer: EMAG  AG
Category: otc | Type: HUMAN OTC DRUG LABEL
Date: 20241203

ACTIVE INGREDIENTS: Sodium Fluoride 110 mg/75 mL
INACTIVE INGREDIENTS: Water; Sorbitol; Hydrated Silica; Propylene Glycol; Sodium C14-16 Olefin Sulfonate; CARBOXYMETHYLCELLULOSE SODIUM, UNSPECIFIED; Saccharin Sodium; Methylparaben Sodium; Titanium Dioxide

Emmi®-dent Kids

Drug Facts

Active Ingredient

Sodium Fluoride 0.11% (0.06% w/v fluoride ion)

Purpose

Anticavity toothpaste

Use

helps protect against cavities

Warning

Keep out of reach of children under 6 yrs. of age.

If more than used for dental cleaning is accidentally swallowed, get medical help or contact a Poison Control Center right away.

Directions

- adults and children 2 yrs. & older: clean teeth thoroughly after meals or at least twice a day or use as directed by a dentist
- do not swallow
- to minimize swallowing use a pea-sized amount in children unter 6
- supervise children's dental cleaning until good habits are established
- children under 2 yrs.: ask a dentist

Inactive ingredients

agua, sorbitol, hydrated silica, propylene glycol, sodium C-14-16 olefin sulfonate, cellulose gum, aroma, sodium saccharin, sodium methylparaben, CI 77891

Questions?

1-561-463-6120

Distributed by D&P Sales Services Group, LLC, Florida, 33332
www.emmident-ultrasound.com
CustomerService@emmident-ultrasound.com

PRINCIPAL DISPLAY PANEL - 75 mL Tube

KIDS

emmi®-dent

Ultrasound Toothpaste

Made in Germany